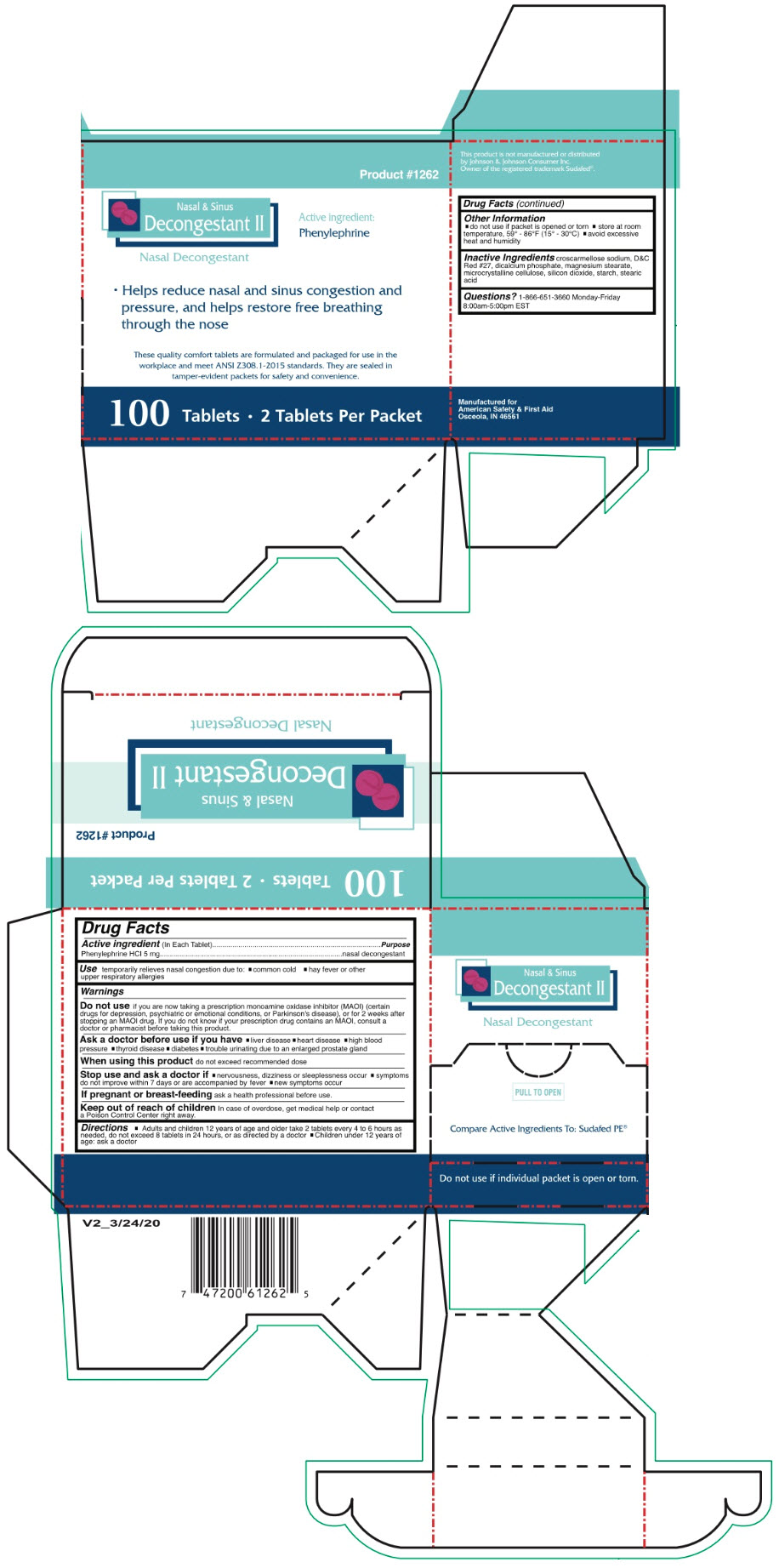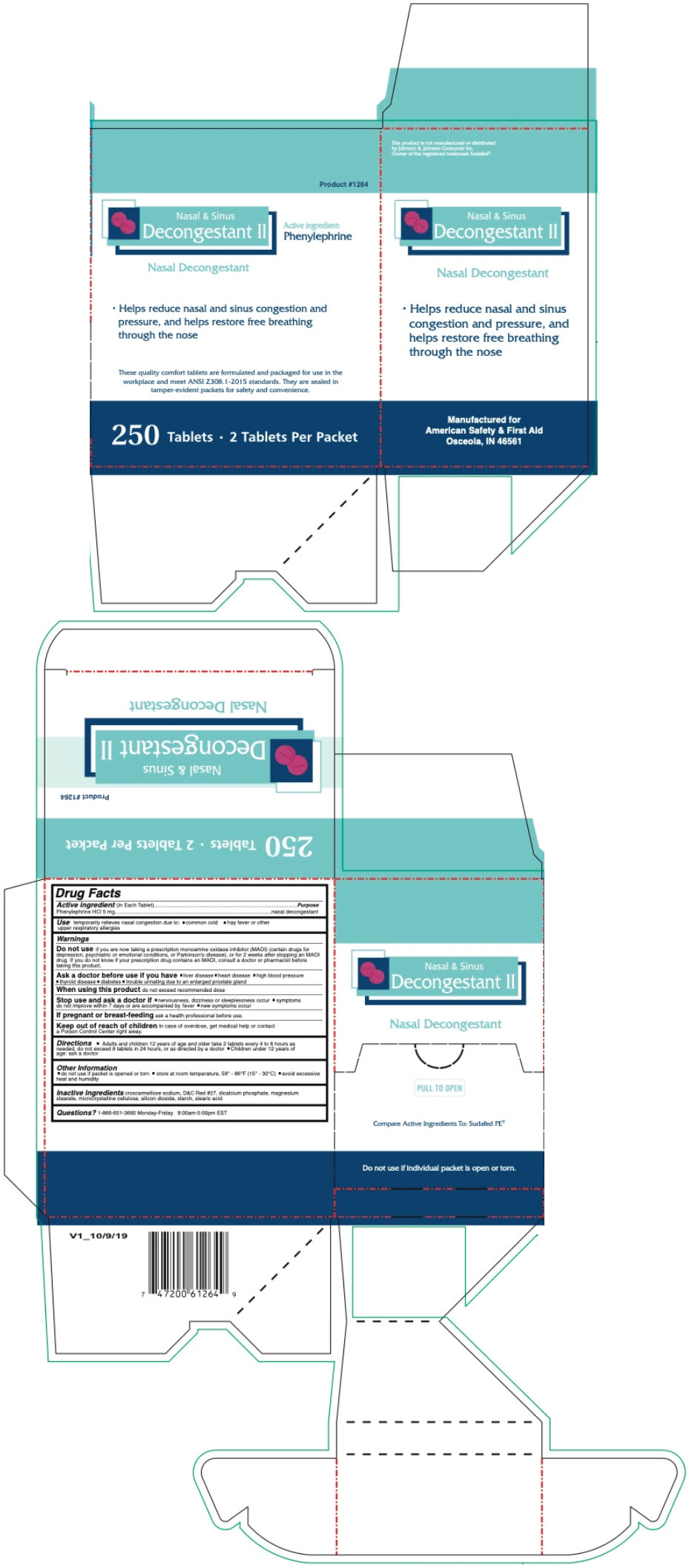 DRUG LABEL: NASAL and SINUS DECONGESTANT
NDC: 73598-1262 | Form: TABLET
Manufacturer: JHK Inc dba American Safety & First Aid
Category: otc | Type: HUMAN OTC DRUG LABEL
Date: 20240426

ACTIVE INGREDIENTS: PHENYLEPHRINE HYDROCHLORIDE 5 mg/1 1
INACTIVE INGREDIENTS: CROSCARMELLOSE SODIUM; D&C RED NO. 27; ANHYDROUS DIBASIC CALCIUM PHOSPHATE; MAGNESIUM STEARATE; MICROCRYSTALLINE CELLULOSE; SILICON DIOXIDE; STARCH, CORN; STEARIC ACID

NASAL AND SINUS DECONGESTANT II

Drug Facts

Active ingredient (In Each Tablets)

Phenylephrine HCl 5 mg

Purpose

nasal decongestant

Use

temporarily relieves nasal congestion due to:

- common cold
- hay fever or other upper respiratory allergies

Warnings

Do not use if you are now taking a prescription monoamine oxidase inhibitor (MAOI) (certain drugs for depression, psychiatric or emotional conditions, or Parkinson's disease), or for 2 weeks after stopping an MAOI drug. If you do not know if your prescription drug contains an MAOI, consult a doctor or pharmacist before taking this product.

Ask a doctor before use if you have

- liver disease
- heart disease
- high blood pressure
- thyroid disease
- diabetes
- trouble urinating due to an enlarged prostate gland

When using this product do not exceed recommended dose

Stop use and ask a doctor if

- nervousness, dizziness or sleeplessness occur
- symptoms do not improve within 7 days or are accompanied by fever
- new symptoms occur

PREGNANCY OR BREAST FEEDING

If pregnant or breast-feeding ask a health professional before use.

Keep out of reach of children In case of overdose, get medical help or contact a Poison Control Center right away.

Directions

- Adults and children 12 years of age and older take 2 tablets every 4 to 6 hours as needed, do not exceed 8 tablets in 24 hours, or as directed by a doctor
- Children under 12 years of age: ask a doctor

Other Information

- do not use if packet is opened or torn
- store at room temperature, 59° - 86°F (15° - 30°C)
- avoid excessive heat and humidity

Inactive Ingredients

croscarmellose sodium, D&C Red #27, dicalcium phosphate, magnesium stearate, microcrystalline cellulose, silicon dioxide, starch, stearic acid

Questions?

1-866-651-3660 Monday-Friday

8:00am-5:00pm EST

PRINCIPAL DISPLAY PANEL - 100 Tablet Box

Product #1262

Nasal & Sinus
Decongestant II

Nasal Decongestant

Active ingredient:
Phenylephrine

- Helps reduce nasal and sinus congestion and
  pressure, and helps restore free breathing
  through the nose

These quality comfort tablets are formulated and packaged for use in the
workplace and meet ANSI Z308.1-2015 standards. They are sealed in
tamper-evident packets for safety and convenience.

100 Tablets • 2 Tablets Per Packet

PRINCIPAL DISPLAY PANEL - 250 Tablet Box

Product #1264

Nasal & Sinus
Decongestant II

Nasal Decongestant

Active ingredient:
Phenylephrine

- Helps reduce nasal and sinus congestion and
  pressure, and helps restore free breathing
  through the nose

These quality comfort tablets are formulated and packaged for use in the
workplace and meet ANSI Z308.1-2015 standards. They are sealed in
tamper-evident packets for safety and convenience.

250 Tablets • 2 Tablets Per Packet